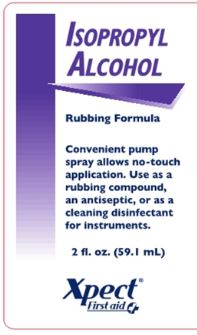 DRUG LABEL: Xpect Isopropyl Alcohol
NDC: 42961-201 | Form: SPRAY
Manufacturer: Cintas Corp
Category: otc | Type: HUMAN OTC DRUG LABEL
Date: 20250922

ACTIVE INGREDIENTS: ISOPROPYL ALCOHOL 70 mL/100 mL
INACTIVE INGREDIENTS: WATER

Active ingredients

Isopropyl Alcohol 70.0%

Purpose

First Aid Antiseptic

Uses

First aid to help prevent infection in minor cuts, scrapes and burns

Warnings

For external use only

Flammable keep away from fire or flame

Do not use

- in eyes or apply over large areas of the body
- longer than 1 week unless directed by a doctor

Ask a doctor before use if you have

- deep or puncture wounds
- animal bites
- serious burns

Stop use and ask a doctor if

- Condition persists or gets worse

Keep out of reach of children. If swallowed, get medical help or contact a Poison Control Center right away.

Directions

- clean the affected area
- spray a small amount 1 to 3 times daily
- may be covered with a sterile bandage.
- if bandaged, let dry first

Other information

- store at room temperature

Inactive Ingredients

purified water

Questions?

1-877-973-2811 M-F 8am-5pm

Principal Display Panel

Isopropyl Alcohol

Rubbing Formula

Convenient pump spray allows no-touch application. Use as a rubbing compound, an antiseptic, or as a cleaning disinfectant for instruments.

2 fl. oz. (59.1 mL)

Xpect® First aid